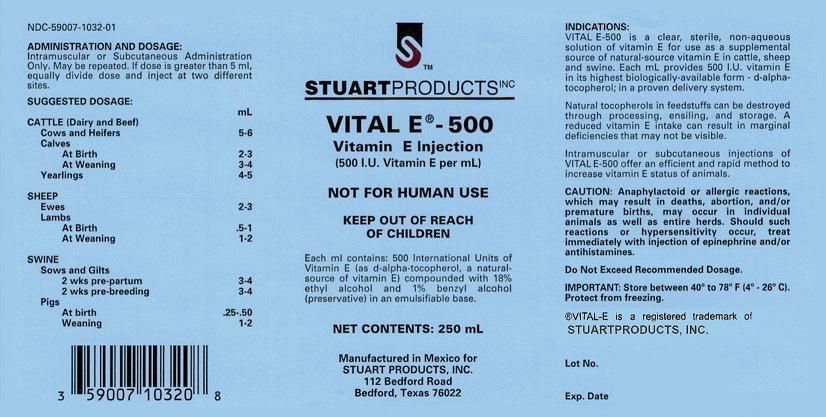 DRUG LABEL: Vital E -
NDC: 59007-1032 | Form: INJECTION, EMULSION
Manufacturer: Stuart Products, Inc.
Category: animal | Type: OTC ANIMAL DRUG LABEL
Date: 20151014

ACTIVE INGREDIENTS: ALPHA-TOCOPHEROL, D- 500 [iU]/1 mL
INACTIVE INGREDIENTS: ALCOHOL 180 1/1 mL; BENZYL ALCOHOL 10 1/1 mL

INDICATIONS:

VITAL E–500 is a clear, sterile, non-aqueous solution of Vitamin E for use as a supplemental source of natural-source vitamin E in cattle, sheep, and swine. Each mL provides 500 I.U. vitamin E in it's highest biologically-available form - d-alpha-tocopherol; in a proven delivery system.

Natural tocopherols can be destroyed in feedstuffs through processing, ensiling, and storage. A reduced vitamin E intake can result in marginal deficiencies that may not be visible.

Intramuscular or subcutaneous injections of VITAL E-500 offer an efficient and rapid method to increase vitamin E status of animals.

ADMINISTRATION AND DOSAGE:

Intramuscular or Subcutaneous Adminstration Only. May be repeated. If dose is greater than 5 mL, equally divide dose and inject at two different sites.

SUGGESTED DOSAGE:

CATTLE (Dairy and Beef)

Cows and Heifers 5-6 mL

Calves

At Birth 2-3 mL

At Weaning 3-4 mL

Yearlings 4-5 mL

SHEEP

Ewes 2-3 mL

Lambs

At Birth: .5-1 mL

At Weaning 1-2 mL

SWINE

Sows and Gilts

2 wks pre-partum 3-4 mL

2 wks pre-breeding 3-4 mL

Pigs

At births .25-.50 mL

Weaning: 1-2 mL

PRECAUTIONS

CAUTION: Anaphylactoid or allergic reactions, which may result in deaths, abortion, and/or premature births, may occur in individual animals as well as entire herds. Should such reactions or hypersensitivity occur, treat immediately with injection of epinephrine and/or antihistamines.

Do Not Exceed Recommended Dosage.

STORAGE AND HANDLING

IMPORTANT: Stored between 40° to 78° F (4°-26°C). Protect from freezing.

®VITAL-E is a registered trademark of

STUARTPRODUCTS, INC.

Principal Display Panel - 250 mL Bottle

STUART PRODUCTS INC

VITAL E® - 500

Vitamin E Injection

(500 I.U. Vitamin E per mL)

NOT FOR HUMAN USE

KEEP OUT OF REACH OF CHILDREN

Each ml contains: 500 International Units of Vitamin E (as d-alpha-tocopherol, a natural-source of Vitamin E) compounded with 18% ethyl alcohol and 1% benzyl alcohol (preservative) in an emulsifiable base.

NET CONTENTS: 250 mL

Manufactured in Mexico for

STUART PRODUCTS, INC.

112 Bedford Road

Bedford, Texas 76022